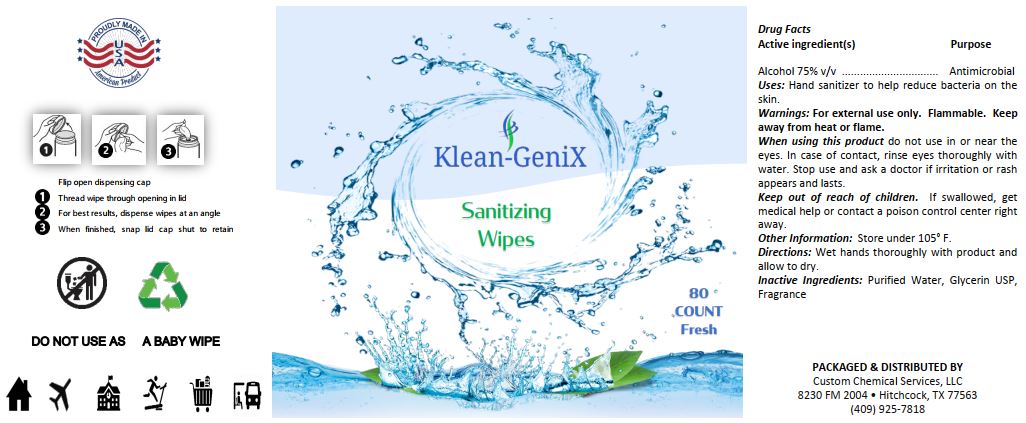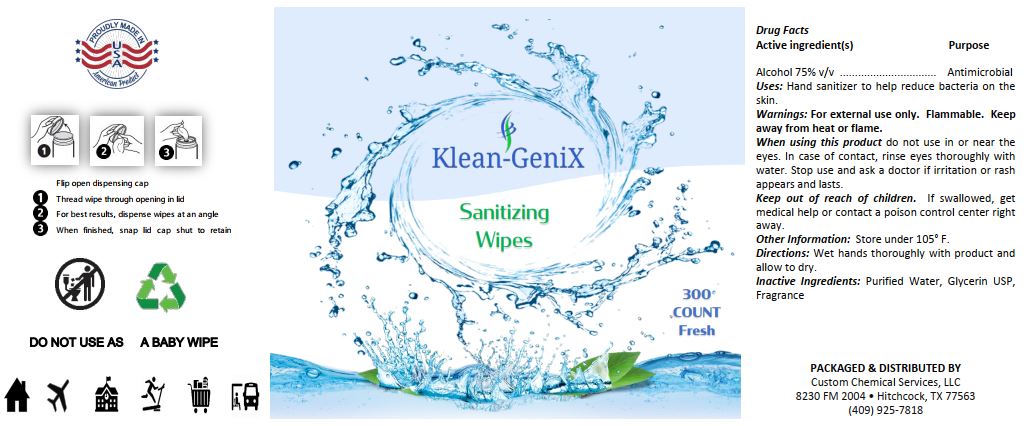 DRUG LABEL: Klean GeniX Sanitizing Wipes Fresh
NDC: 78174-048 | Form: CLOTH
Manufacturer: Custom Chemical Services, LLC
Category: otc | Type: HUMAN OTC DRUG LABEL
Date: 20210427

ACTIVE INGREDIENTS: ALCOHOL 70.1038 L/100 L
INACTIVE INGREDIENTS: GLYCERIN 0.0678 L/100 L; water 29.6218 L/100 L; FRAGRANCE CUCUMBER ALOE ORC1802955 0.2066 1/100 L

Active Ingredients

Alcohol 75% v/v

Purpose

Antimicrobial

INDICATIONS AND USAGE

Uses Hand sanitizer to help reduce bacteria on the skin.

WARNINGS

Warnings: For external use only. Flammable. Keep away from fire or flame.

When using this product do not use in or near the eyes. In case of contact, rinse eyes thoroughly with water. Stop use and ask a doctor if irritation or rash appears and lasts.

Keep out of reach of children. If swallowed, get medical help or contact a poison control center right away.

Other Information Store under 105°F.

DOSAGE AND ADMINISTRATION

Directions: Wet hands thoroughly with product and allow to dry.

Inactive Ingredients Purified water, Glycerin USP, Fragrance

PACKAGE LABEL

08 – 37.5 oz (80 count):

09 – 52.5 oz (300 count):